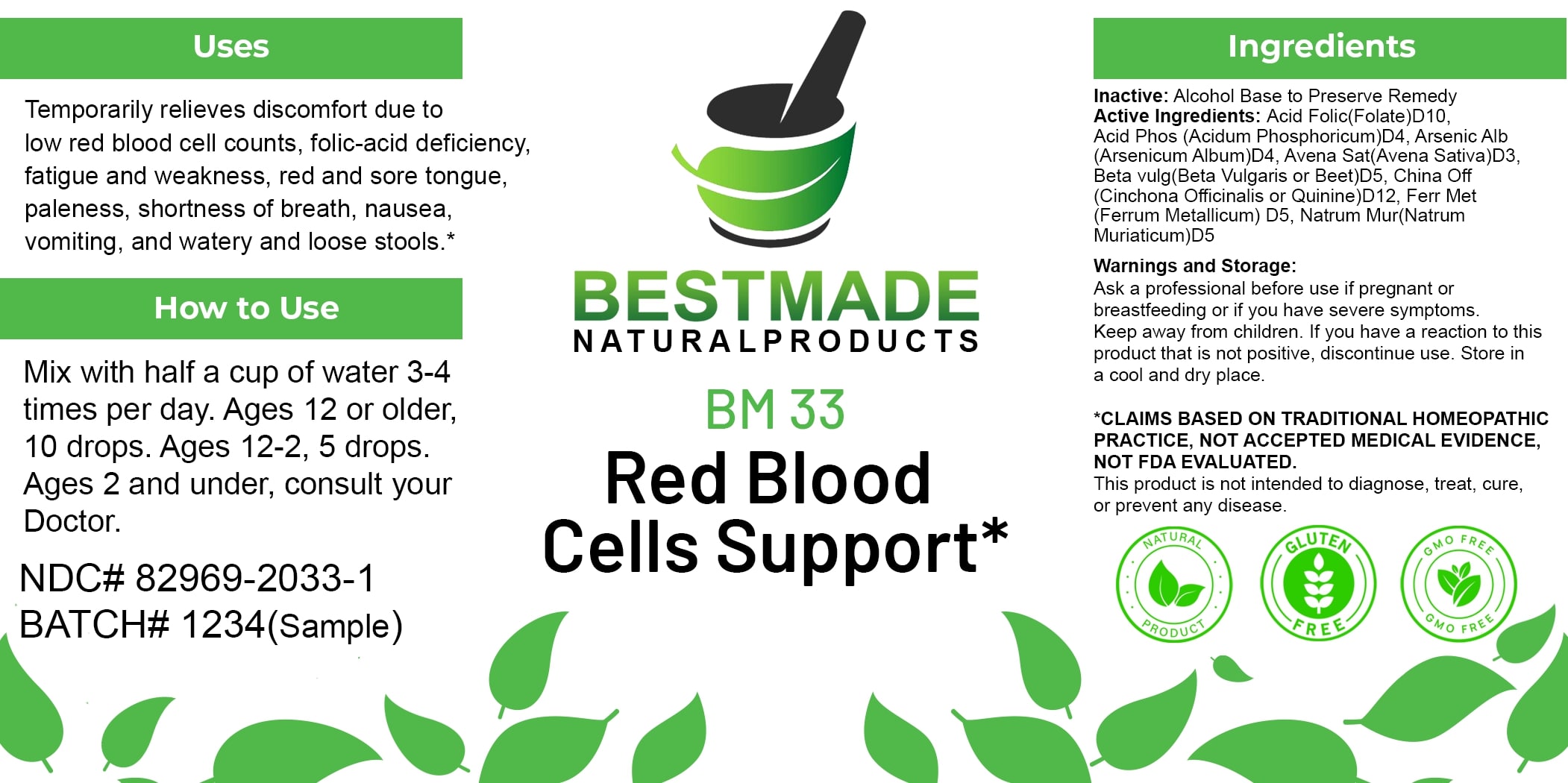 DRUG LABEL: Bestmade Natural Products BM33
NDC: 82969-2033 | Form: LIQUID
Manufacturer: Bestmade Natural Products
Category: homeopathic | Type: HUMAN OTC DRUG LABEL
Date: 20250123

ACTIVE INGREDIENTS: SODIUM CHLORIDE 30 [hp_C]/30 [hp_C]; FOLIC ACID 30 [hp_C]/30 [hp_C]; CINCHONA OFFICINALIS BARK 30 [hp_C]/30 [hp_C]; PHOSPHORIC ACID 30 [hp_C]/30 [hp_C]; AVENA SATIVA FLOWERING TOP 30 [hp_C]/30 [hp_C]; IRON 30 [hp_C]/30 [hp_C]; ARSENIC TRIOXIDE 30 [hp_C]/30 [hp_C]; BETA VULGARIS 30 [hp_C]/30 [hp_C]
INACTIVE INGREDIENTS: ALCOHOL 30 [hp_C]/30 [hp_C]

BM33

DOSAGE AND ADMINISTRATION

How to Use

Mix with half a cup of water 3-4 times per day. Ages 12 or older, 10 drops. Ages 12-2, 5 drops. Ages 2 and under, consult your Doctor.

INACTIVE INGREDIENT

Ingredients

Inactive: Alcohol Base to Preserve Remedy

Uses

Temporarily relieves discomfort due to low red blood cell counts, folic-acid deficiency, fatigue and weakness, red and sore tongue, paleness, shortness of breath, nausea, vomiting, and watery and loose stools.*

*CLAIMS BASED on TRADITIONAL HOMEOPATHIC PRACTICE, NOT ACCEPTED MEDICAL EVIDENCE, NOT FDA EVALUATED.

This product is not intended to diagnose, treat, cure, or prevent any disease.

Uses

Temporarily relieves discomfort due to low red blood cell counts, folic-acid deficiency, fatigue and weakness, red and sore tongue, paleness, shortness of breath, nausea, vomiting, and watery and loose stools.*

*CLAIMS BASED on TRADITIONAL HOMEOPATHIC PRACTICE, NOT ACCEPTED MEDICAL EVIDENCE, NOT FDA EVALUATED.

This product is not intended to diagnose, treat, cure, or prevent any disease.

ACTIVE INGREDIENT

Active Ingredients: Acid Folic (Folate) D10, Acid Phos (Acidum Phosphoricum) D4, Arsenic Alb (Arsenicum Album) D4, Avena Sat (Avena Sativa) D3, Beta vulg (Beta Vulgaris or Beet) D5, China Off (Cinchona Officinalis or Quinine) D12, Ferr Met (Ferrum Metallicum) D5, Natrum Mur (Natrum Muriaticum) D5

KEEP OUT OF REACH OF CHILDREN

Warnings and Storage:

Ask a professional before use if pregnant or breastfeeding or if you have severe symptoms. Keep away from children. If you have a reaction to this product that is not positive, discontinue use. Store in a cool and dry place.

Warnings and Storage:

Ask a professional before use if pregnant or breastfeeding or if you have severe symptoms. Keep away from children. If you have a reaction to this product that is not positive, discontinue use. Store in a cool and dry place.

*CLAIMS BASED on TRADITIONAL HOMEOPATHIC PRACTICE, NOT ACCEPTED MEDICAL EVIDENCE, NOT FDA EVALUATED.

This product is not intended to diagnose, treat, cure, or prevent any disease.

Entire package label